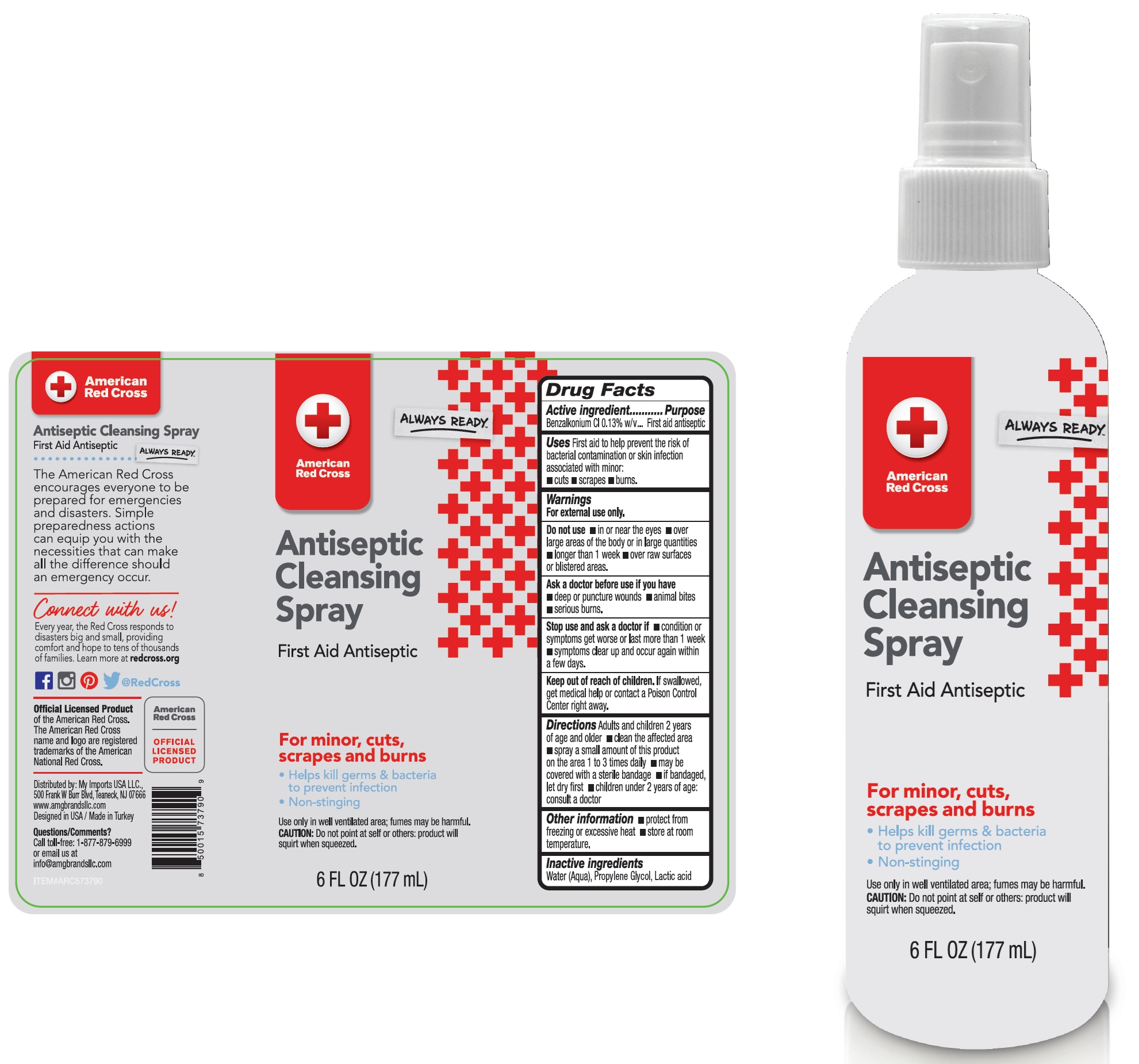 DRUG LABEL: American Red Cross Antiseptic Cleansing
NDC: 51628-0035 | Form: SPRAY
Manufacturer: MY IMPORTS USA, LLC
Category: otc | Type: HUMAN OTC DRUG LABEL
Date: 20251202

ACTIVE INGREDIENTS: BENZALKONIUM CHLORIDE 1.3 mg/1 mL
INACTIVE INGREDIENTS: WATER; PROPYLENE GLYCOL; LACTIC ACID

American Red Cross Antiseptic Cleansing Spray

Active ingredient

Benzalkonium Cl 0.13% w/v

Purpose

First aid antiseptic

Uses

First aid to help prevent the risk of bacterial contamination or skin infection associated with minor: • cuts • scrapes • burns.

Warnings

For external use only.

Do not use

• in or near the eyes
• over large areas of the body or in large quantities
• longer than I week
• over raw surfaces or blistered areas.

Ask a doctor before use if you have

• deep or puncture wounds •animal bites • serious burns.

Stop use and ask a doctor if

• condition or symptoms get worse or last more than I week
• symptoms clear up and occur again within a few days.

Keep out of reach of children.

If swallowed, get medical help or contact a Poison Control Center right away.

Directions

Adults and children 2 years of age and older • clean the affected area • spray a small amount of this product on the area 1 to 3 times daily • may be covered with a sterile bandage • if bandaged, let dry first • children under 2 years of age: consult a doctor

Other information

• protect from freezing or excessive heat • store at room temperature.

Inactive ingredients

Water (Aqua), Propylene Glycol, Lactic acid